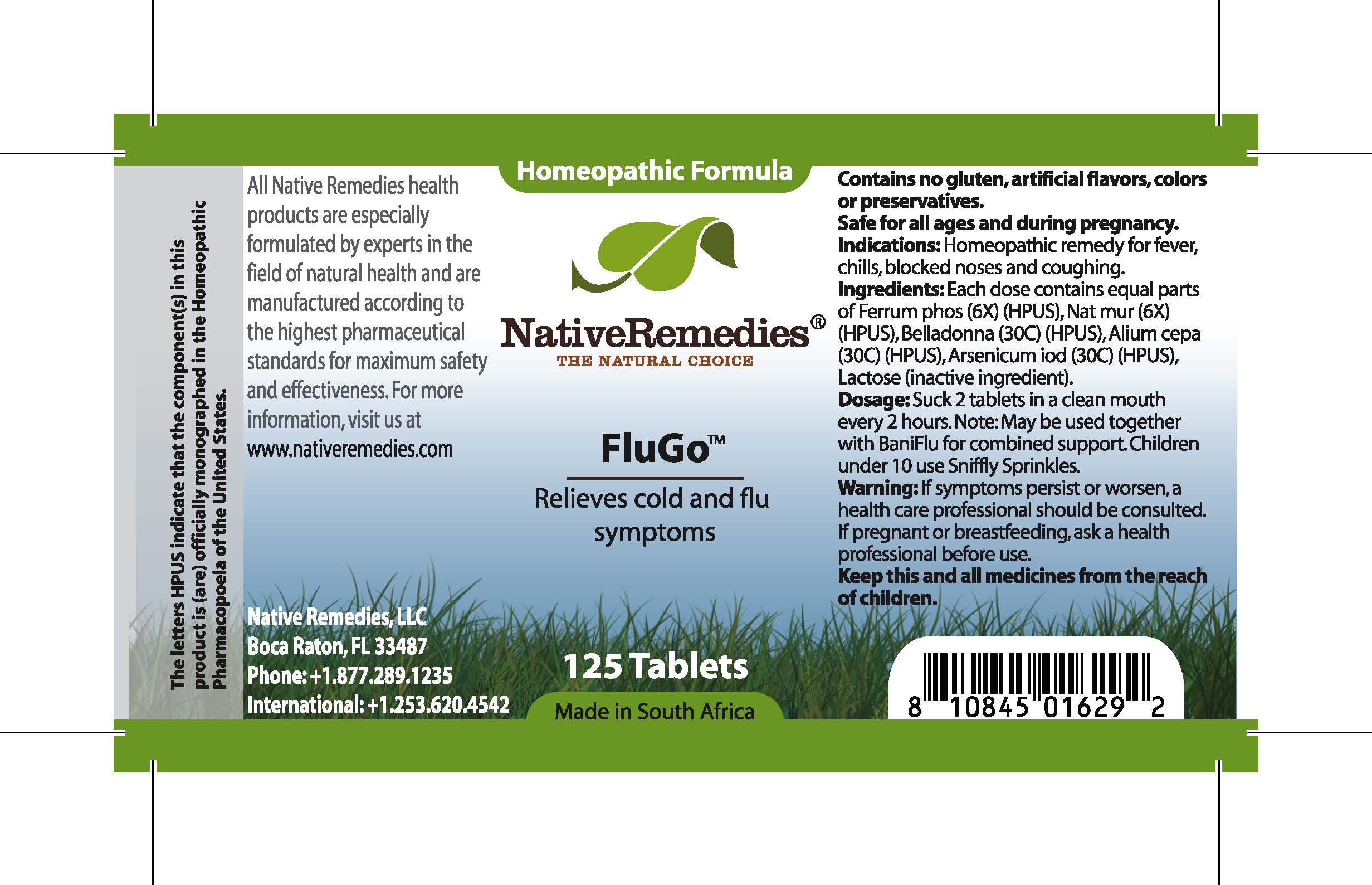 DRUG LABEL: FluGo
NDC: 68647-117 | Form: TABLET
Manufacturer: Feelgood Health
Category: homeopathic | Type: HUMAN OTC DRUG LABEL
Date: 20100712

ACTIVE INGREDIENTS: FERRUM PHOSPHORICUM 6 [hp_X]/1 1; SODIUM CHLORIDE 6 [hp_X]/1 1; ATROPA BELLADONNA ROOT 30 [hp_C]/1 1; ONION 30 [hp_C]/1 1; ARSENIC TRIIODIDE 30 [hp_C]/1 1
INACTIVE INGREDIENTS: LACTOSE

FLUGO

DESCRIPTION

Relieves cold and flu symptoms

INDICATIONS AND USAGE

Indications: Homeopathic remedy for fever, chills, blocked noses and coughing.

DOSAGE AND ADMINISTRATION

Dosage: Dissolve 2 tablets in a clean mouth every 2 hours. May be used together with BaniFlu™ for combined support. Children under 10 use Sniffly Sprinkles™.

GENERAL PRECAUTIONS

Caution: If symptoms persist or worsen, a health care professional should be consulted. Keep this and all medicines from the reach of children.

ACTIVE INGREDIENT

Ingredients: Each dose contains equal parts of Ferrum phos (6X) (HPUS), Nat mur (6X) (HPUS), Belladonna (30C) (HPUS), Alium cepa (30C) (HPUS), Arsenicum iod (30C) (HPUS)

Lactose (inactive ingredient).

PREGNANCY

If pregnant or breastfeeding, ask a health professional before use.

USER SAFETY WARNINGS

Contains no gluten, artificial flavors, colors or preservatives. Safe for all ages and during pregnancy.

PATIENT COUNSELING INFORMATION

All Native Remedies health products are especially formulated by experts in the field of natural health and are manufactured according to the highest pharmaceutical standards for maximum safety and effectiveness. For more information, visit us at www.nativeremedies.com

Distributed by

Native Remedies, LLC

6531 Park of Commerce Blvd.

Suite 160

Boca Raton, FL 33487

Phone: 1.877.289.1235

International: + 1.561.999.8857

The letters HPUS indicate that the component(s) in this product is (are) officially monographed in the Homeopathic Pharmacopoeia of the United States.